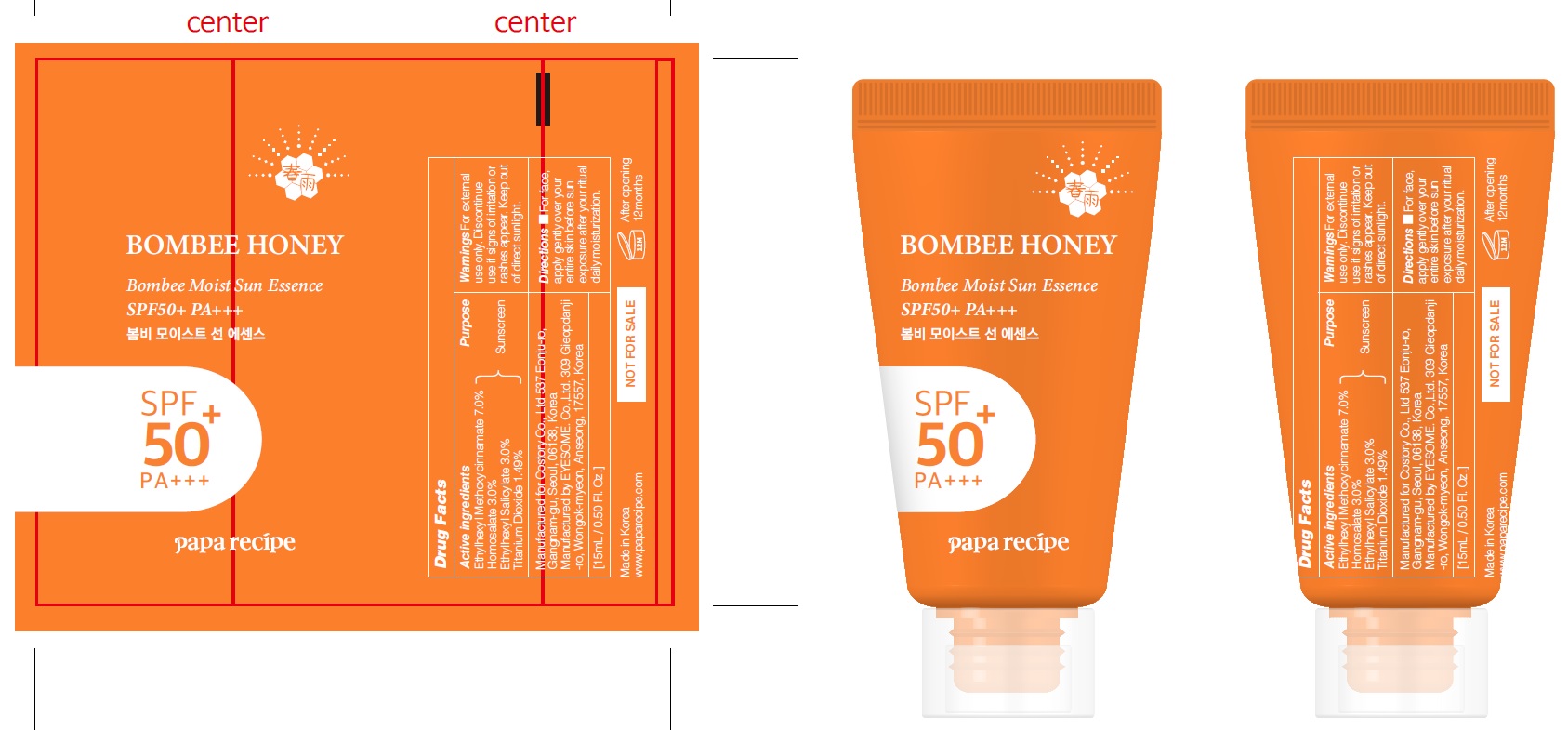 DRUG LABEL: PAPA RECIPE BOMBEE MOIST SUN ESSENCE
NDC: 73020-080 | Form: CREAM
Manufacturer: Costory Co., Ltd
Category: otc | Type: HUMAN OTC DRUG LABEL
Date: 20210105

ACTIVE INGREDIENTS: Octinoxate 1.05 g/15 mL; Homosalate 0.45 g/15 mL; Octisalate 0.45 g/15 mL; Titanium Dioxide 0.22 g/15 mL
INACTIVE INGREDIENTS: Water; Alcohol

ACTIVE INGREDIENTS

Ethylhexyl Methoxycinnamate 7.0%, Homosalate 3.0%, Ethylhexyl Salicylate 3.0%, Titanium Dioxide 1.49%

INACTIVE INGREDIENTS

Water, Alcohol, Pentylene Glycol, Bis-Ethylhexyloxyphenol Methoxyphenyl Triazine, Caprylyl Methicone, 1,2-Hexanediol, Glycerin, Isononyl Isononanoate, Ethylhexyl Triazone, Polyglyceryl-3 Methylglucose Distearate, Lauryl Methacrylate/Glycol Dimethacrylate Crosspolymer, Ammonium Acryloyldimethyltaurate/VP Copolymer, Cyclopentasiloxane, Sodium Acrylate/Sodium Acryloyldimethyl Taurate Copolymer, Dimethicone/Vinyl Dimethicone Crosspolymer, Aluminum Hydroxide, Stearic Acid, Isohexadecane, Xanthan Gum, Tocopheryl Acetate, Sorbitan Isostearate, Ethylhexylglycerin, Allantoin, Limonene, Polysorbate 80, Sorbitan Oleate, Butylene Glycol, Citrus Limon (Lemon) Peel Oil, Sodium Hyaluronate, Rosa Damascena Flower Extract, Nelumbo Nucifera Flower Extract, Carthamus Tinctorius (Safflower) Flower Extract, Camellia Japonica Flower Extract, Citral, Honey Extract, Propolis Extract, Royal Jelly Extract, Sophora Japonica Fruit Extract, Ethyl Hexanediol, Lavandula Angustifolia (Lavender) Flower Extract, Viola Tricolor Extract, Centaurea Cyanus Flower Extract, Pancratium Maritimum Extract, Caprylyl Glycol

PURPOSE

Sunscreen

WARNINGS

For external use only. Discontinue use if signs of irritation or rashes appear. Keep out of direct sunlight.

Directions

■ For face, apply gently over your entire skin before sun exposure after your ritual daily moisturization.